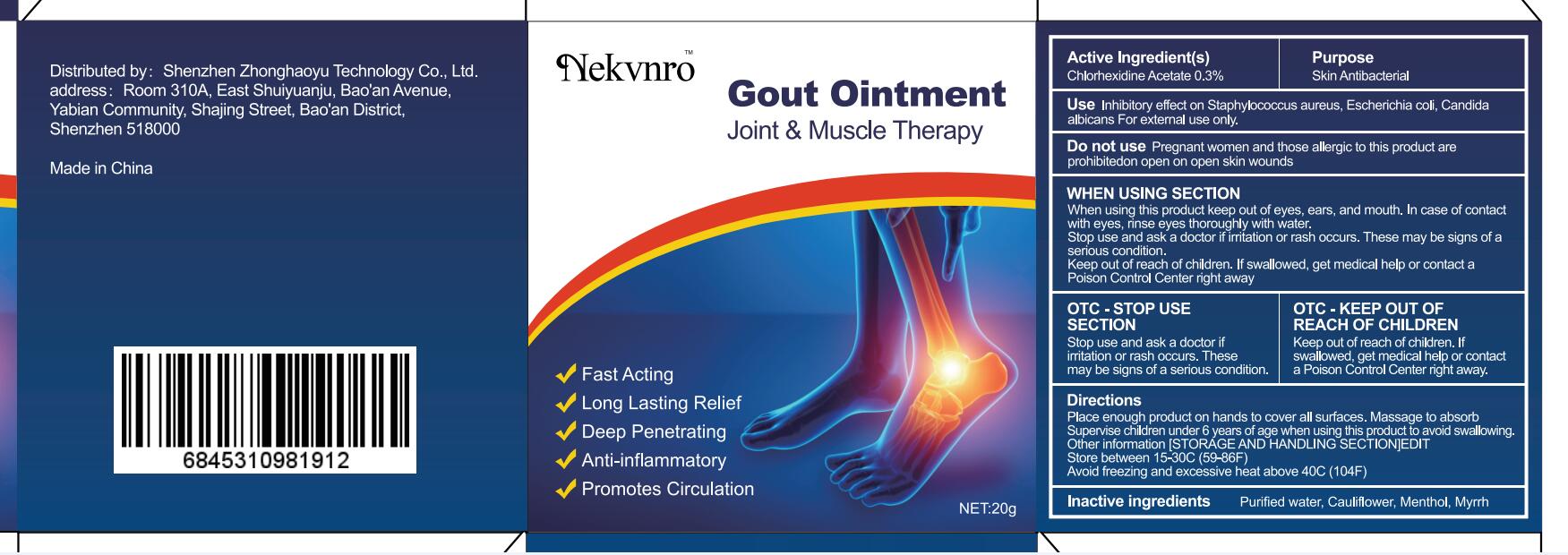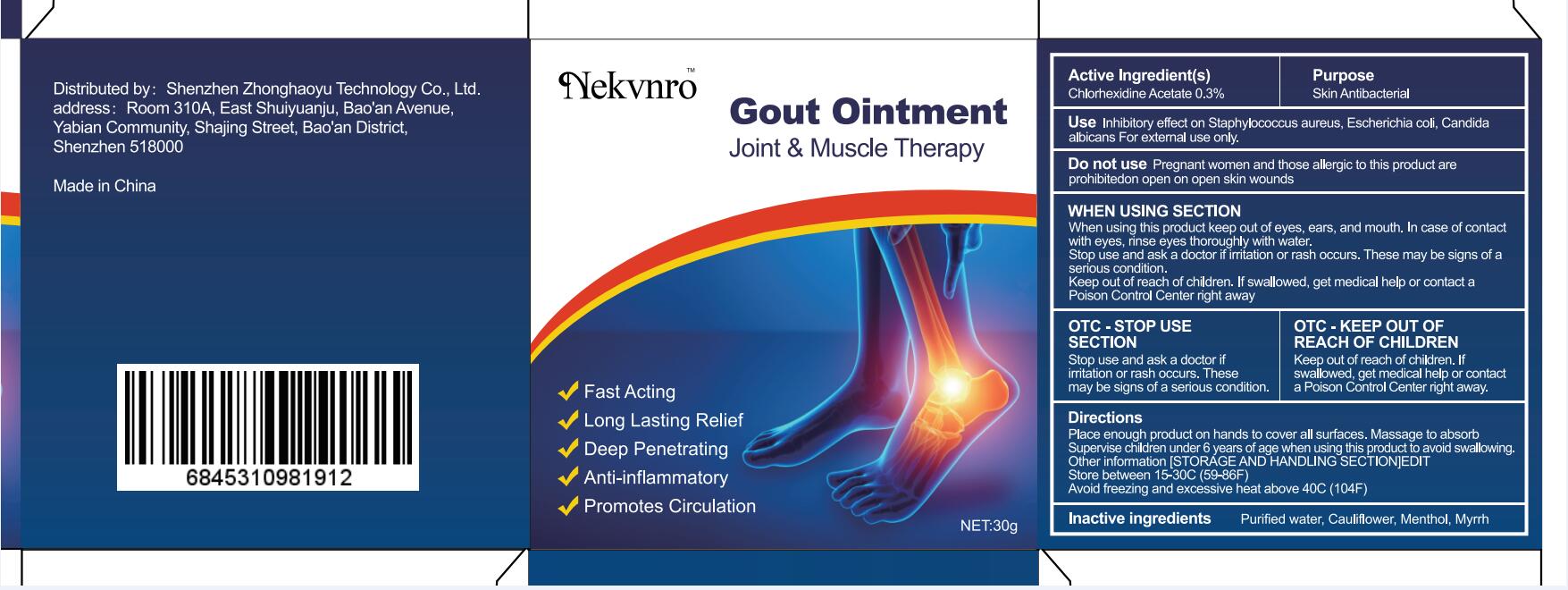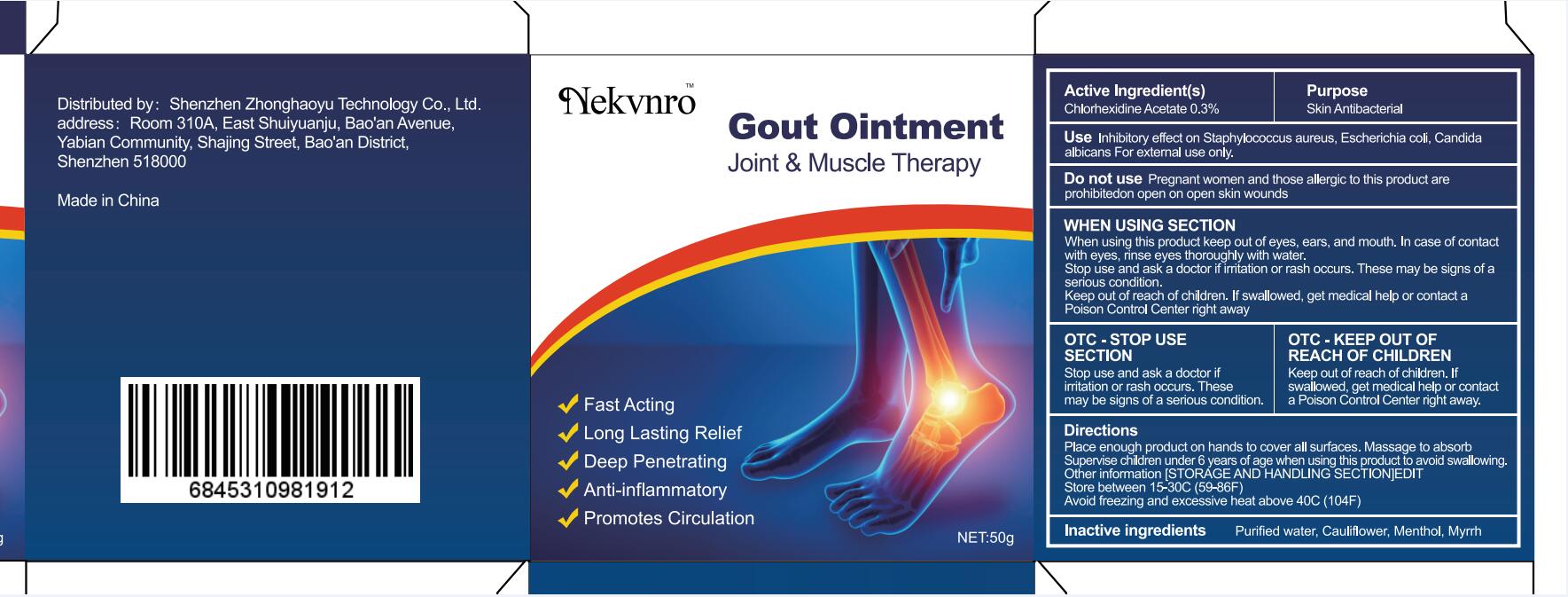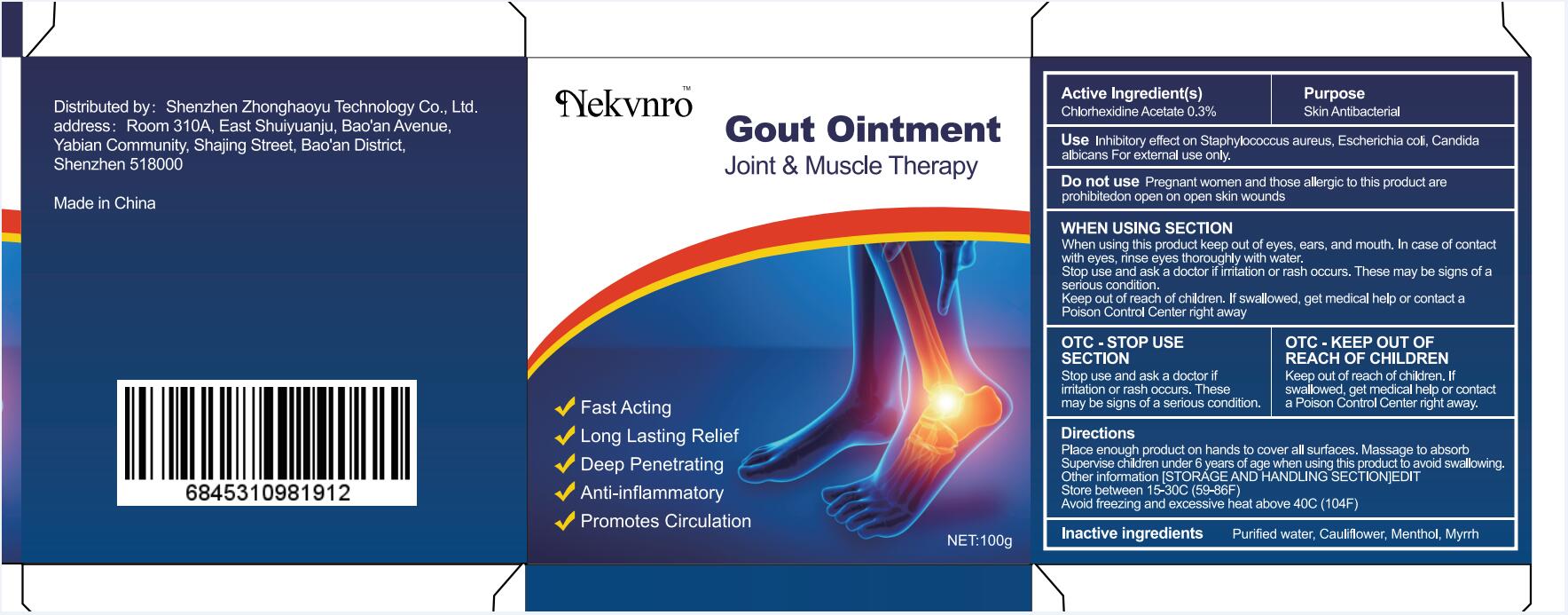 DRUG LABEL: Gout
NDC: 82877-001 | Form: OINTMENT
Manufacturer: Shenzhen Boceda New Technology Co., Ltd.
Category: homeopathic | Type: HUMAN OTC DRUG LABEL
Date: 20220706

ACTIVE INGREDIENTS: CHLORHEXIDINE ACETATE 0.03 g/100 g
INACTIVE INGREDIENTS: WATER; CAULIFLOWER; MENTHOL; MYRRH

82877-001 Gout Ointment

Active Ingredient(s)

Chlorhexidine Acetate 0.3%

Purpose

Skin Antibacterial

Use

Inhibitory effect on Staphylococcus aureus, Escherichia coli, Candida albicans For external use only.

Do not use

Pregnant women and those allergic to this product are prohibitedon open on open skin wounds

WHEN USING SECTION

When using this product keep out of eyes, ears, and mouth. In case of contact with eyes, rinse eyes thoroughly with water.

Stop use and ask a doctor if irritation or rash occurs. These may be signs of a serious condition.

Keep out of reach of children. If swallowed, get medical help or contact a Poison Control Center right away

OTC - STOP USE SECTION

Stop use and ask a doctor if iritation or rash occurs.These may be signs of a serious condition.

OTC - KEEP OUT OF REACH OF CHILDREN

Keep out of reach of children. If swallowed, get medical help or contac a Poison Control Center right away.

Directions

Place enough product on hands to cover all surfaces. Massage to absorb Supervise children under 6 years of age when using this product to avoid swallowing.

Other information

[STORÁGE AND HANDLING SECTION]EDIT

Store between 15-30C (59-86F)

Avoid freezing and excessive heat above 40C (104F)

Inactive ingredients

Purified water, Cauliflower, Menthol, Myrrh

Warnings

Keep out of reach of children. If swallowed, get medical help or contact a Poison Control Center right away